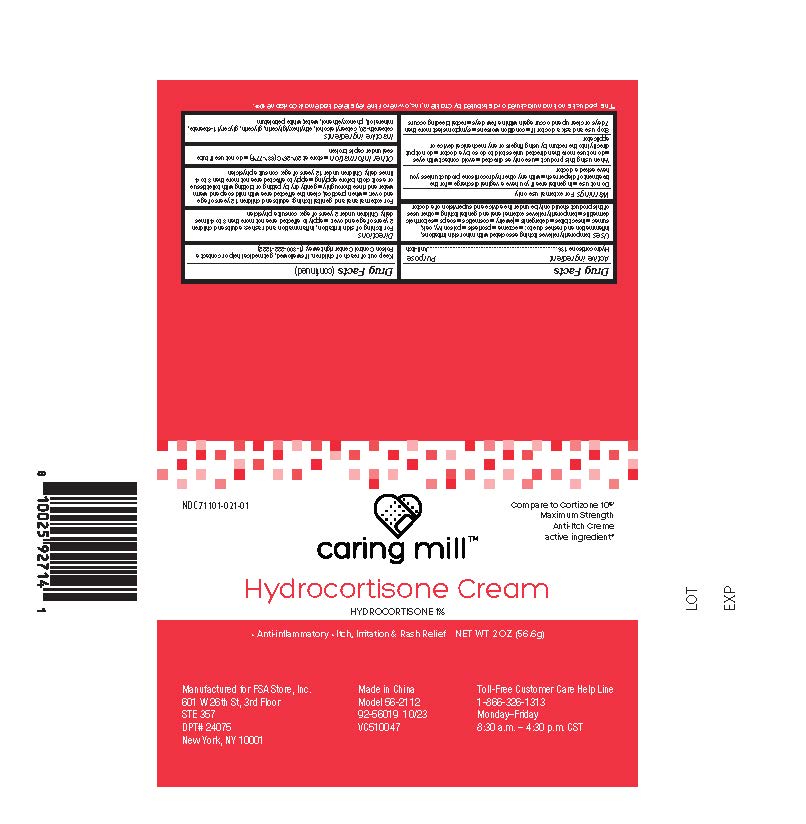 DRUG LABEL: Caring Mills Hydrocortisone
NDC: 71101-021 | Form: CREAM
Manufacturer: Veridian Healthcare
Category: otc | Type: HUMAN OTC DRUG LABEL
Date: 20251222

ACTIVE INGREDIENTS: HYDROCORTISONE 1 g/100 g
INACTIVE INGREDIENTS: CETOSTEARYL ALCOHOL; CETEARETH-20; PHENOXYETHANOL; ETHYLHEXYLGLYCERIN; GLYCERYL 1-STEARATE; MINERAL OIL; WHITE PETROLATUM; WATER; GLYCERIN

Caring Mills Hydrocortisone Cream 2 oz

Active Ingredient:

Hydrocortisone 1%

Purpose

Anti-itch

Uses

- temporarily relieves itching associated with minor skin irritations, inflammation, and rashes due to:
  - eczema
  - psoriasis
  - poison ivy, oak, sumac
  - insect bites
  - detergents
  - jewelry
  - cosmetics
  - soaps
  - seborrheic dermatitis
  - temporarily relieves external anal and genital itching
  - other uses of this product should only be under the advice and supervision of a doctor

Warnings

For external use only

Do not use

- in the genital area if you have a vaginal discharge.
- for the treatment of diaper rash.
- with any other hydrocortisone product unless you have asked a doctor

When using this product

- use only as directed
- avoid contact with eyes
- do not use more than directed unless told to do so by a doctor
- do not put directly into the rectum by using fingers or any mechanical device or applicator

Stop use and ask a doctor if

- condition worsens, symptoms persist for more than 7 days or clear up and occur again within a few days, and do not begin use of any other hydrocortisone product unless you have asked a doctor
- rectal bleeding occurs

Keep out of reach of children.

If swallowed, get medical help or contact a Poison Control Center right away. (1-800-222-1222)

Directions

- for itching of skin irritation, inflammation, and rashes:
- adults and children 2 years of age and over: apply to affected area not more than 3 to 4 times daily
- children under 2 years of age: consult a physician
- for external anal and genital itching, adults and children 12 years of age and over:
  - when practical, clean the affected area with mild soap and warm water and rinse thoroughly
  - gently dry by patting or blotting with toilet tissue or a soft cloth before applying
  - apply to affected area not more than 3 to 4 times daily
  - children under 12 years of age: consult a physician

Other information

Store at 20-25C (68-77F)

do not use if tube seal under cap is broken

Inactive Ingredients

ceteareth-20, cetearyl alcohol, ethylhexylglycerin, glycerin, glyceryl 1-stearate, mineral oil, phenoxyethanol, water, white petrolatum